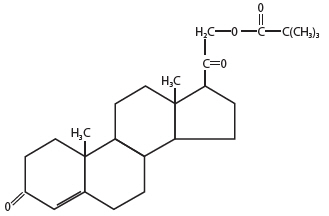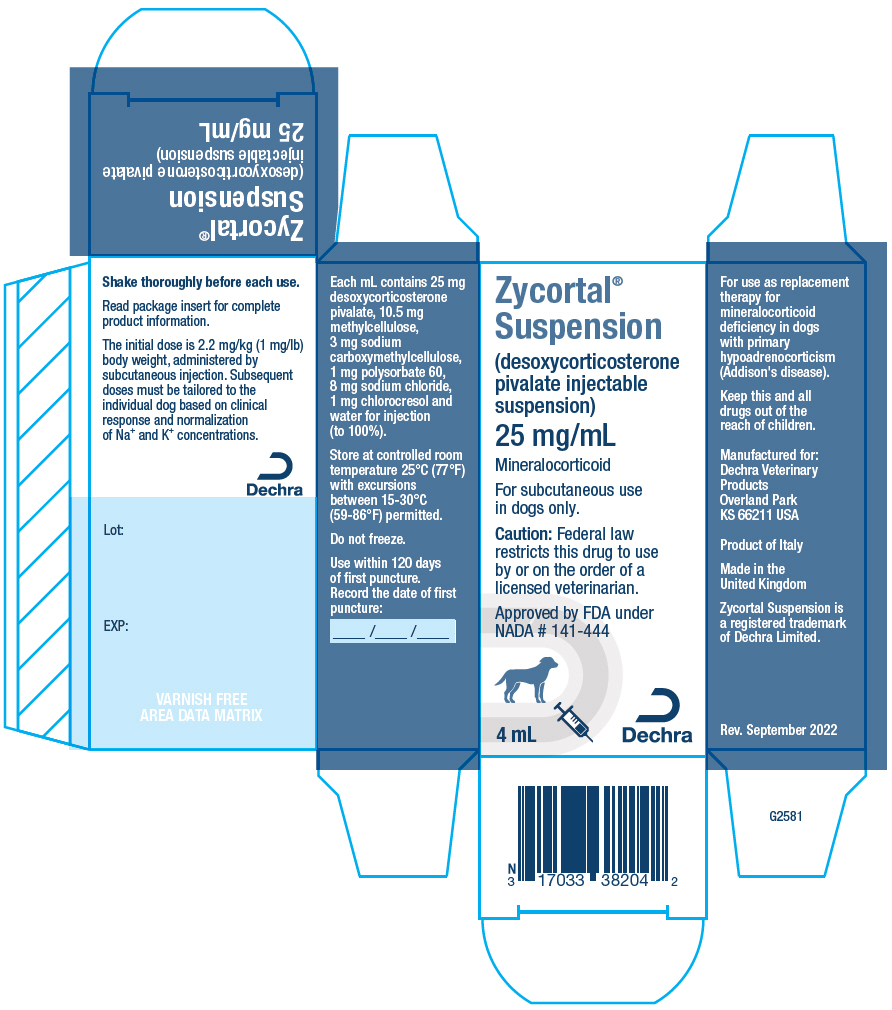 DRUG LABEL: ZYCORTAL
NDC: 17033-382 | Form: INJECTION, SUSPENSION
Manufacturer: Dechra Veterinary Products
Category: animal | Type: PRESCRIPTION ANIMAL DRUG LABEL
Date: 20230727

ACTIVE INGREDIENTS: DESOXYCORTICOSTERONE PIVALATE 25 mg/1 mL

Zycortal® Suspension
(desoxycorticosterone pivalate injectable suspension)

For subcutaneous use in dogs only

Mineralocorticoid

CAUTION:

Federal law (U.S.A.) restricts this drug to use by or on the order of a licensed veterinarian.

DESCRIPTION:

Desoxycorticosterone pivalate is a mineralocorticoid hormone. Chemically, desoxycorticosterone pivalate is 21-(2,2-dimethyl-1-oxopropoxy)-pregn-4-ene-3,20-dione.

The structural formula is:

Molecular Formula: C26H38O4

ZYCORTAL Suspension is a white aqueous suspension. Each milliliter contains 25 mg of desoxycorticosterone pivalate. Inactive ingredients are 10.5 mg methylcellulose, 3 mg sodium carboxymethylcellulose, 1 mg polysorbate 60, 8 mg sodium chloride, 1 mg chlorocresol and water for injection (to 100%).

INDICATION:

For use as replacement therapy for mineralocorticoid deficiency in dogs with primary hypoadrenocorticism (Addison's disease).

DOSAGE AND ADMINISTRATION:

Prior to each use, thoroughly shake the vial to resuspend the product.

ZYCORTAL Suspension replaces the mineralocorticoid hormones only. Dogs with combined glucocorticoid and mineralocorticoid deficiency should also be treated with prednisone or prednisolone at an initial dosage of 0.2-0.4 mg/kg/day (0.1-0.2 mg/lb/day).

ZYCORTAL Suspension is intended for long-term administration at intervals and doses dependent upon individual response. Tailor the dose of ZYCORTAL Suspension and the concurrently administered glucocorticoid replacement therapy to the individual dog based on clinical response and normalization of Na^+ and K^+ concentrations.

Initial dose of ZYCORTAL Suspension:

The initial dose is 2.2 mg/kg (1 mg/lb) body weight, administered by subcutaneous injection.

Interim monitoring visit:

Re-evaluate the dog and measure the serum sodium/potassium ratio (Na^+/K^+ ratio) approximately 10 days after the first dose, which is the time to maximum concentration (Tmax) of desoxycorticosterone (see CLINICAL PHARMACOLOGY). If the dog's clinical signs have worsened or not resolved, adjust the dose of prednisone/prednisolone and/or investigate other causes of the clinical signs.

Second dose of ZYCORTAL Suspension:

At approximately 25 days after the first dose, re-evaluate the dog and repeat the Na^+/K^+ ratio.

- If the dog is both clinically normal and has a normal Na^+/K^+ ratio on Day 25, adjust the dose based on the Day 10 Na^+/K^+ ratio using the guidelines in Table 1, below.
- If the dog is clinically normal and has a Na^+/K^+ ratio > 32 on Day 25, either adjust the dose based on the Day 10 Na^+/K^+ ratio according to Table 1 or delay the dose (see Prolonging the dosing interval).
- If the dog is either not clinically normal or if the Na^+/K^+ ratio is abnormal on Day 25, adjust the dose of prednisone/prednisolone or ZYCORTAL Suspension (see Subsequent doses and long-term management).

Table 1: Day 25: Administering the Second Dose of ZYCORTAL Suspension
If the Day 10 Na^+/K^+ ratio is: | Do not administer Dose 2 on Day 10. | 25 days after the first dose, administer ZYCORTAL Suspension, as follows:
> 34 | Do not administer Dose 2 on Day 10. | Decrease dose to: 2.0 mg/kg
> 32 to 34 | Do not administer Dose 2 on Day 10. | Decrease dose to: 2.1 mg/kg
27 to 32 | Do not administer Dose 2 on Day 10. | Continue 2.2 mg/kg
24 to < 27 | Do not administer Dose 2 on Day 10. | Increase dose to: 2.3 mg/kg
< 24 | Do not administer Dose 2 on Day 10. | Increase dose to: 2.4 mg/kg

Prolonging the dosing interval:

If the dog is clinically normal and the Day 25 Na^+/K^+ ratio is > 32, it is possible to prolong the dosing interval instead of adjusting the dose as described in Table 1. Evaluate the electrolytes every 3-7 days until the Na^+/K^+ ratio is < 32, and then administer 2.2 mg/kg of ZYCORTAL Suspension.

Subsequent doses and long-term management:

For subsequent doses, use the following guidelines if the dog is not clinically normal and/or has abnormal Na^+ or K^+ concentrations:

- Clinical signs of polyuria/polydipsia: Decrease the prednisone/prednisolone dose first. If the polyuria/polydipsia persists, then decrease the dose of ZYCORTAL Suspension without changing the dosing interval.
- Clinical signs of depression, lethargy, vomiting, diarrhea or weakness: Increase prednisone/prednisolone dose.
- Hyperkalemia, hyponatremia or Na^+/K^+ ratio < 27: Decrease the ZYCORTAL Suspension dosing interval by 2-3 days.
- Hypokalemia or hypernatremia: Decrease the ZYCORTAL Suspension dose.

Prior to a stressful situation, consider temporarily increasing the dose of prednisone/prednisolone.

CONTRAINDICATIONS:

Do not use ZYCORTAL Suspension in dogs that have previously had a hypersensitivity reaction to desoxycorticosterone pivalate.

WARNINGS:

Use ZYCORTAL Suspension with caution in dogs with congestive heart disease, edema, severe renal disease or primary hepatic failure. Desoxycorticosterone pivalate may cause polyuria, polydipsia, increased blood volume, edema and cardiac enlargement. Excessive weight gain may indicate fluid retention secondary to sodium retention.

Do not use desoxycorticosterone pivalate in pregnant dogs.

HUMAN WARNINGS:

Not for human use. Keep this and all drugs out of the reach of children. Consult a physician in case of accidental human exposure.

PRECAUTIONS:

Any dog presenting with severe hypovolemia, dehydration, pre-renal azotemia and inadequate tissue perfusion ("Addisonian crisis") must be rehydrated with intravenous fluid (saline) therapy before starting treatment with ZYCORTAL Suspension.

The effectiveness of ZYCORTAL Suspension may be reduced if potassium-sparing diuretics, such as spironolactone, are administered concurrently.

ADVERSE REACTIONS:

In controlled clinical field studies, one hundred fifty-two dogs were included in the field safety analysis. Adverse reactions are summarized in Table 2.

Table 2: Percentage of Dogs with Adverse Reactions in the Field Study
Adverse Reaction | ZYCORTAL Suspension (n = 113 dogs) | Active Control (n = 39 dogs)
Polyuria | 15.0% (17) | 12.8% (5)
Polydipsia | 13.3% (15) | 15.4% (6)
Depression/lethargy | 9.7% (11) | 2.6% (1)
Inappropriate urination | 8.0% (9) | 10.3% (4)
Alopecia | 5.3% (6) | 5.1% (2)
Decreased appetite/anorexia | 4.4% (5) | 2.6% (1)
Panting | 3.5% (4) | 0.0% (0)
Vomiting | 3.5% (4) | 0.0% (0)
Diarrhea | 2.7% (3) | 7.7% (3)
Shaking/trembling | 2.7% (3) | 2.6% (1)
Polyphagia | 1.8% (2) | 2.6% (1)
Urinary tract infection | 1.8% (2) | 0.0% (0)
Urinary incontinence | 0.9% (1) | 2.6% (1)
Restlessness | 0.9% (1) | 2.6% (1)
Urticaria/facial edema | 0.0% (0) | 5.1% (2)

One dog with a pre-existing Grade III/VI heart murmur developed congestive heart failure 17 days after the first administration of ZYCORTAL Suspension and was removed from the study.

Post-Approval Experience (2020)

The following adverse events are based on post approval adverse drug experience reporting for ZYCORTAL Suspension. Not all adverse events are reported to FDA/CVM. It is not always possible to reliably estimate the adverse event frequency or establish a causal relationship to product exposure using these data.

The following adverse events in dogs are listed in decreasing order of reporting frequency:

Injection site pain, lethargy, vomiting, polydipsia, anorexia, polyuria, diarrhea, weight gain, alopecia, anaphylaxis, collapse, and anemia.

Death or euthanasia has been associated with some of the adverse events listed above.

To report suspected adverse events, for technical assistance or to obtain a copy of the safety data sheet (SDS), contact Dechra at (866) 933-2472.

For additional information about adverse drug experience reporting for animal drugs, contact the FDA at 1-888-FDA-VETS or http://www.fda.gov/reportanimalae.

CLINICAL PHARMACOLOGY:

Desoxycorticosterone is a corticosteroid with primarily mineralocorticoid activity, similar to aldosterone. In the kidney, desoxycorticosterone causes sodium and chloride ion retention, and hydrogen and potassium ion excretion, creating an osmotic gradient. The osmotic gradient promotes water absorption from the renal tubules resulting in increased extracellular fluid volume, leading to blood volume expansion, improved venous return to the heart, and increased cardiac output.

After subcutaneous administration of 11 mg/kg body weight (five times the labeled starting/initial dose of 2.2 mg/kg) of ZYCORTAL Suspension, the plasma half-life (mean ± standard deviation) is approximately 17 ± 7 days, with a maximum concentration (Cmax) of 13.2 ± 5 ng/mL, and time to maximum concentration (Tmax) of 10 ± 3.5 days.

EFFECTIVENESS:

A double-blinded, multi-site, 180-day field study evaluated the effectiveness of ZYCORTAL Suspension compared to an FDA-approved desoxycorticosterone pivalate active control. One hundred fifty-two (152) dogs of various breeds, 0.5-12.4 years of age and weighing 0.95-61.2 kg were enrolled. One hundred thirteen (113) dogs were treated with ZYCORTAL Suspension and 39 dogs were treated with the active control. Both groups were administered an initial dose of 2.2 mg/kg. Subsequent doses administered and/or frequency of administration were adjusted according to the clinical needs of the dog.

A dog was considered a treatment success if it remained clinically normal or had improved clinical signs compared to baseline and the Na^+ and K^+ concentrations were within the reference range of the analyzer, or the Na^+/K^+ ratio was between 27-32. Success rates for ZYCORTAL Suspension were 86.2% and 88.3% on Days 90 and 180, respectively; success rates for the active control were 85.1% and 86.9% on Days 90 and 180, respectively.

The mean final dose for ZYCORTAL Suspension was 1.9 ± 0.27 mg/kg (range 1.2-2.5 mg/kg) and the mean final dose interval was 38.5 ± 12.5 days (range 20-99 days) with the majority of dogs having a dosing interval between 20 and 46 days.

ANIMAL SAFETY:

In a laboratory study, ZYCORTAL Suspension was administered via subcutaneous injection to 32 Beagle dogs (four groups of 8 dogs each) at doses of 0, 1, 3 and 5 times the labeled starting dose (1× = 2.2 mg/kg), once every 21 days for 6 months, for a total of 9 injections. The volume injected in 3× and 5× dogs was equally divided between three and five sites, respectively. Dogs in the 1× group were dosed at a single injection site. Control dogs (0×) received subcutaneous injections of 0.9% sodium chloride at a volume equivalent to the 5× dose.

The most frequently noted abnormal clinical observations were injection site reactions in treated dogs, characterized by erythema and edema. Clinical pathology findings considered related to ZYCORTAL Suspension treatment included: decreased mean corpuscular volume in 3× and 5× groups; increased globulin concentrations in all treated groups; decreased potassium concentrations in all treated groups; increased sodium concentrations in all treated groups; decreased chloride concentrations in the 3× group; decreased blood urea nitrogen concentrations in all treated groups; and decreased urine specific gravity concentrations in all treated groups. Gross necropsy findings considered treatment-related included: subcapsular and cortical renal cysts, corresponding histologically with vascular tunica media hyperplasia; and irregular white plaques in the injection site subcutaneous tissue, corresponding histologically with granulomatous inflammation. Additional histology findings considered treatment-related included: chronic inflammation of the renal cortices, cortical tubular basophilia, cortical tubular dilation, glomerulopathy (3× and 5× groups), and adrenal gland vacuolation (zona glomerulosa).

STORAGE INFORMATION:

Store at controlled room temperature 25°C (77°F) with excursions between 15-30°C (59-86°F) permitted.

Do not freeze.

Use within 120 days of first puncture.

HOW SUPPLIED:

ZYCORTAL Suspension is supplied in a clear glass vial with 4 mL (100 mg) desoxycorticosterone pivalate (25 mg/mL).

Approved by FDA under NADA # 141-444

Manufactured for:
Dechra Veterinary Products, 7015 College Boulevard, Suite
525, Overland Park, KS 66211 USA

ZYCORTAL is a registered trademark of Dechra Limited.

F2128
Rev. September 2022

PRINCIPAL DISPLAY PANEL - 4 mL Vial Carton

Zycortal®
Suspension

(desoxycorticosterone
pivalate injectable
suspension)

25 mg/mL

Mineralocorticoid

For subcutaneous use
in dogs only.

Caution: Federal law
restricts this drug to use
by or on the order of a
licensed veterinarian.

Approved by FDA under
NADA # 141-444

4 mL

Dechra